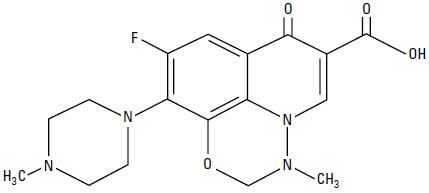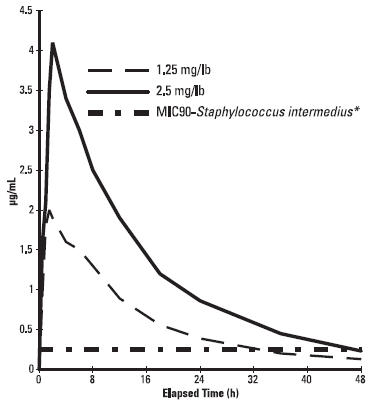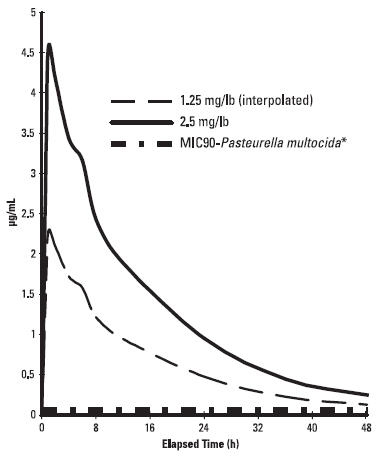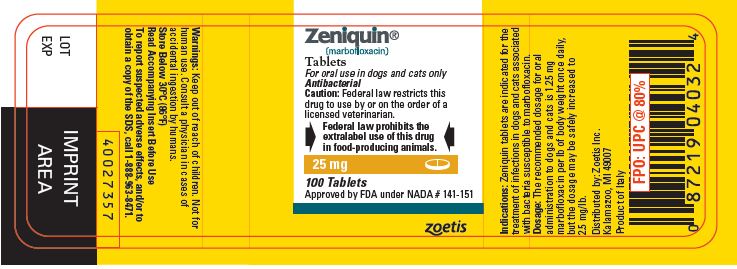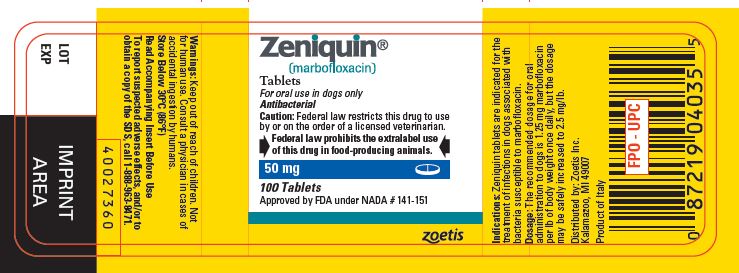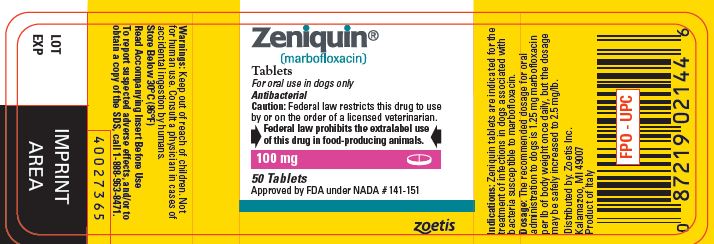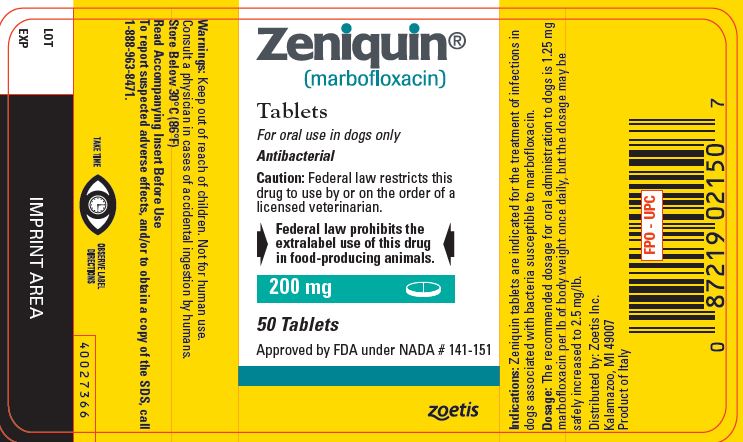 DRUG LABEL: Zeniquin
NDC: 54771-8485 | Form: TABLET
Manufacturer: Zoetis Inc.
Category: animal | Type: PRESCRIPTION ANIMAL DRUG LABEL
Date: 20191002

ACTIVE INGREDIENTS: MARBOFLOXACIN 25 mg/1 1

Zeniquin®
(marbofloxacin)

Tablets

For oral use in dogs and cats only

CAUTION: Federal law restricts this drug to use by or on the order of a licensed veterinarian.

Federal law prohibits the extralabel use of this drug in food-producing animals.

DESCRIPTION

Marbofloxacin is a synthetic broad-spectrum antibacterial agent from the fluoroquinolone class of chemotherapeutic agents. Marbofloxacin is the non-proprietary designation for 9-fluoro-2,3-dihydro-3-methyl-10-(4-methyl-1-piperazinyl)-7-oxo-7H-pyrido[3,2,1-ij][4,1,2] benzoxadiazine-6-carboxylic acid. The empirical formula is C17H19FN4O4 and the molecular weight is 362.36. The compound is soluble in water; however, solubility decreases in alkaline conditions. The N-octanol/water partition coefficient (Kow) is 0.835 measured at pH 7 and 25°C.

Figure 1: Chemical structure of marbofloxacin

CLINICAL PHARMACOLOGY

Marbofloxacin is rapidly and almost completely absorbed from the gastrointestinal tract following oral administration to fasted animals. Divalent cations are generally known to diminish the absorption of fluoroquinolones. The effects of concomitant feeding on the absorption of marbofloxacin have not been determined. (See Drug Interactions.) In the dog, approximately 40% of an oral dose of marbofloxacin is excreted unchanged in the urine^1. Excretion in the feces, also as unchanged drug, is the other major route of elimination in dogs. Ten to 15% of marbofloxacin is metabolized by the liver in dogs.

In vitro plasma protein binding of marbofloxacin in dogs was 9.1% and in cats was 7.3%. In the cat, approximately 70% of an oral dose is excreted in the urine as marbofloxacin and metabolites with approximately 85% of the excreted material as unchanged drug. Pharmacokinetic parameters related to intravenous dosing were estimated in a study of 6 healthy adult beagle dogs, and are summarized in Table 1. The absolute bioavailability following dosing of oral tablets to the same animals was 94%.

Marbofloxacin plasma concentrations were determined over time in healthy adult beagle dogs (6 dogs per dosage group) following single oral doses of 1.25 mg/lb or 2.5 mg/lb. Absorption of orally administered marbofloxacin increases proportionally over the dose range of 1.25 to 2.5 mg/lb. Marbofloxacin plasma concentrations were determined over time in 7 healthy adult male cats following a single oral dose of 2.5 mg/lb. Plasma pharmacokinetic parameters following oral dosing of dogs and cats are summarized in Figures 2 and 3 and in Table 2. Based on the terminal elimination half-life and the dosing interval, steady-state levels are reached after the third dose and are expected to be approximately 25% greater in dogs and 35% greater in cats than those achieved after a single dose. Marbofloxacin is widely distributed in canine tissues. Tissue concentrations of marbofloxacin were determined in healthy male beagle dogs (4 dogs per time period) at 2, 18 and 24 hours after a single oral dose (1.25 or 2.5 mg/lb) and are summarized in Tables 3a and 3b.

Table 1: Mean pharmacokinetic parameters following intravenous administration of marbofloxacin to 6 adult beagle dogs at a dosage of 2.5 mg/lb.

Parameter | Estimate ± SD* n=6
Total body clearance, (mL/h•kg) | 94 ± 8
Volume of distribution at steady state, Vss, (L/kg) | 1.19 ± 0.08
AUC0-inf (μg•h/mL) | 59 ± 5
Terminal plasma elimination half-life, t1/2(h) | 9.5 ± 0.7

* SD = standard deviation

Table 2: Mean pharmacokinetic parameters following oral administration of marbofloxacin tablets to adult beagle dogs at a nominal dosage of 1.25 mg/lb or
2.5 mg/lb and to cats at 2.5 mg/lb.†

Parameters | Dog Estimate ± SD* (1.25 mg/lb) n=6 | Dog Estimate ± SD* (2.5 mg/lb) n=6 | Cat Estimate ± SD* (2.5 mg/lb) n=7
Time of maximum concentration, Tmax(h) | 1.5 ± 0.3 | 1.8 ± 0.3 | 1.2 ± 0.6
Maximum concentration, Cmax, (μg/mL) | 2.0 ± 0.2 | 4.2 ± 0.5 | 4.8 ± 0.7
AUC0-inf (μg•h/mL) | 31.2 ± 1.6 | 64 ± 8 | 70 ± 6
Terminal plasma elimination half-life, t1/2(h) | 10.7 ± 1.6 | 10.9 ± 0.6 | 12.7 ± 1.1

† mean actual dosages administered to dogs were 1.22 mg/lb and 2.56 mg/lb, respectively, and the mean
actual dosage administered to cats was 2.82 mg/lb.
* SD = standard deviation

Figure 2: Mean plasma concentrations (µg/mL) following single oral administration of marbofloxacin to adult beagle dogs at dosages of 1.25 mg/lb or 2.5 mg/lb.

* See Table 4 in Microbiology section for MIC data.

Figure 3: Mean plasma concentrations (µg/mL) following single oral administration of marbofloxacin to adult cats at a dosage of 2.5 mg/lb.

* See Table 5 in Microbiology section for MIC data.

Table 3a: Tissue distribution following a single oral administration of marbofloxacin tablets to adult beagle dogs at a dosage of 1.25 mg/lb*.

Tissue | Marbofloxacin 2 hours (n=4) | Concentrations 18 hours (n=4) | (μg/g ± SD) 24 hours (n=4)
bladder | 4.8 ± 1.1 | 2.6 ± 1.5 | 1.11 ± 0.19
bone marrow | 3.1 ± 0.5 | 1.5 ± 1.5 | 0.7 ± 0.2
feces | 15 ± 9 | 48 ± 40 | 26 ± 11
jejunum | 3.6 ± 0.5 | 1.3 ± 1.0 | 0.7 ± 0.3
kidney | 7.1 ±1.7 | 1.4 ± 0.5 | 0.9 ± 0.3
lung | 3.0 ± 0.5 | 0.8 ± 0.2 | 0.57 ± 0.19
lymph node | 5.5 ± 1.1 | 1.3 ± 0.3 | 1.0 ± 0.3
muscle | 4.1 ± 0.3 | 1.0 ± 0.3 | 0.7 ± 0.2
prostate | 5.6 ± 1.4 | 1.8 ± 0.6 | 1.1 ± 0.4
skin | 1.9 ± 0.6 | 0.41 ± 0.13 | 0.32 ± 0.08

* SD = standard deviation

Table 3b: Tissue distribution following a single oral administration of marbofloxacin tablets to adult beagle dogs at a dosage of 2.5 mg/lb.

Tissue | Marbofloxacin 2 hours (n=4) | Concentrations 18 hours (n=4) | (μg/g ± SD*) 24 hours (n=4)
bladder | 12 ± 4 | 6 ± 7 | 1.8 ± 0.4
bone marrow | 4.6 ± 1.5 | 1.28 ± 0.13 | 0.9 ± 0.3
feces | 18 ± 3 | 52 ± 17 | 47 ± 28
jejunum | 7.8 ± 1.1 | 2.0 ± 0.3 | 1.1 ± 0.3
kidney | 12.7 ±1.7 | 2.7 ± 0.3 | 1.6 ± 0.2
lung | 5.48 ± 0.17 | 1.45 ± 0.19 | 1.0 ± 0.2
lymph node | 8.3 ± 0.7 | 2.3 ± 0.5 | 2.03 ± 0.06
muscle | 7.5 ± 0.5 | 1.8 ± 0.3 | 1.20 ± 0.12
prostate | 11 ± 3 | 2.7 ± 1.0 | 2.0 ± 0.5
skin | 3.20 ± 0.33 | 0.705 ± 0.013 | 0.46 ± 0.09

* SD = standard deviation

Microbiology

The primary action of fluoroquinolones is to inhibit the bacterial enzyme, DNA gyrase. In susceptible organisms, fluoroquinolones are rapidly bactericidal at relatively low concentrations. Marbofloxacin is bactericidal against a broad range of gram-negative and gram-positive organisms. The minimum inhibitory concentrations (MICs) of pathogens isolated in clinical field studies performed in the United States were determined using National Committee for Clinical Laboratory Standards (NCCLS) standards, and are shown in Tables 4 and 5.

Table 4. MIC Values* (μg/mL) of marbofloxacin against pathogens isolated from skin, soft tissue and urinary tract infections in dogs enrolled in clinical studies conducted during 1994–1996.

Organism | No. of Isolates | MIC50 | MIC90 | MIC Range
Staphylococcus intermedius | 135 | 0.25 | 0.25 | 0.125-2
Escherichia coli | 61 | 0.03 | 0.06 | 0.015-2
Proteus mirabilis | 35 | 0.06 | 0.125 | 0.03-0.25
Beta-hemolytic Streptococcus,; (not Group A or Group B) | 25 | 1 | 2 | 0.5-16
Streptococcus,; Group D enterococcus | 16 | 1 | 4 | 0.008-4
Pasteurella multocida | 13 | 0.015 | 0.06 | ≤0.008-0.5
Staphylococcus aureus | 12 | 0.25 | 0.25 | 0.25-0.5
Enterococcus faecalis | 11 | 2 | 2 | 1-4
Klebsiella pneumonia | 11 | 0.06 | 0.06 | 0.01-0.06
Pseudomonas spp. | 9 | ** | ** | 0.06-1
Pseudomonas aeruginosa | 7 | ** | ** | 0.25-1

* The correlation between in vitro susceptibility data (MIC) and clinical response has not been
determined.
** MIC50 and MIC90 not calculated due to insufficient number of isolates.

Table 5: MIC Values* (μg/mL) of marbofloxacin against pathogens isolated from
skin and soft tissue infections in cats enrolled in clinical studies conducted in 1995
and 1998.

Organism | No. of Isolates | MIC50 | MIC90 | MIC Range
Pasteurella multocida | 135 | 0.03 | 0.06 | ≤0.008-0.25
Beta-hemolytic Streptococcus | 22 | 1 | 1 | 0.06-1
Staphylococcus aureus | 21 | 0.25 | 0.5 | 0.125-1
Corynebacterium spp. | 14 | 0.5 | 1 | 0.25-2
Staphylococcus intermedius | 11 | 0.25 | 0.5 | 0.03-0.5
Enterococcus faecalis | 10 | 2.0 | 2.0 | 1.0-2.0
Escherichia coli | 10 | 0.03 | 0.03 | 0.015-0.03
Bacillus spp. | 10 | 0.25 | 0.25 | 0.125-0.25

* The correlation between in vitro susceptibility data (MIC) and clinical response has not been
determined.

INDICATIONS AND USAGE

Zeniquin (marbofloxacin) tablets are indicated for the treatment of infections in dogs and cats associated with bacteria susceptible to marbofloxacin.

CONTRAINDICATIONS

Marbofloxacin and other quinolones have been shown to cause arthropathy in immature animals of most species tested, the dog being particularly sensitive to this side effect. Marbofloxacin is contraindicated in immature dogs during the rapid growth phase (small and medium breeds up to 8 months of age, large breeds up to 12 months of age and giant breeds up to 18 months of age). Marbofloxacin is contraindicated in cats under 12 months of age. Marbofloxacin is contraindicated in dogs and cats known to be hypersensitive to quinolones.

WARNING

For use in animals only. Keep out of reach of children. Avoid contact with eyes. In case of contact, immediately flush eyes with copious amounts of water for 15 minutes. In case of dermal contact, wash skin with soap and water. Consult a physician if irritation persists following ocular or dermal exposure. Individuals with a history of hypersensitivity to fluoroquinolones should avoid this product. In humans, there is a risk of user photosensitization within a few hours after excessive exposure to quinolones. If excessive accidental exposure occurs, avoid direct sunlight.

PRECAUTIONS

Quinolones should be used with caution in animals with known or suspected central nervous system (CNS) disorders. In such animals, quinolones have, in rare instances, been associated with CNS stimulation which may lead to convulsive seizures. Quinolones have been shown to produce erosions of cartilage of weight-bearing joints and other signs of arthropathy in immature animals of various species. The use of fluoroquinolones in cats has been reported to adversely affect the retina. Such products should be used with caution in cats. The safety of marbofloxacin in animals used for breeding purposes, pregnant, or lactating has not been demonstrated.

ADVERSE REACTIONS

The following clinical signs were reported during the course of clinical field studies in dogs receiving marbofloxacin at dosages up to 2.5 mg/lb daily: decreased or loss of appetite (5.4%), decreased activity (4.4%), and vomiting (2.9%). The following signs were reported in less than 1% of cases in dogs: increased thirst, soft stool/diarrhea, behavioral changes, shivering/shaking/tremors, and ataxia. One dog which had a seizure the day before study enrollment experienced a seizure while on marbofloxacin therapy.

The following clinical signs were reported during clinical field studies in cats receiving 1.25 mg/lb/day: diarrhea (2.1%) and soft stool (1.4%). Vomiting was reported in less than 1% of cases in cats.

DOSAGE AND ADMINISTRATION

The recommended dosage for oral administration to dogs and cats is 1.25 mg marbofloxacin per lb of body weight once daily, but the dosage may be safely increased to 2.5 mg/lb.

For the treatment of skin and soft tissue infections, Zeniquin tablets should be given for 2–3 days beyond the cessation of clinical signs for a maximum of 30 days. For the treatment of urinary tract infections, Zeniquin tablets should be administered for at least 10 days. If no improvement is noted within 5 days, the diagnosis should be re-evaluated and a different course of therapy considered.

Drug Interactions

Compounds (e.g., sucralfate, antacids, and mineral supplements) containing divalent and trivalent cations (e.g., iron, aluminum, calcium, magnesium, and zinc) can interfere with the absorption of quinolones which may result in a decrease in product bioavailability. Therefore, the concomitant oral administration of quinolones with foods, supplements, or other preparations containing these compounds should be avoided.

EFFECTIVENESS CONFIRMATION

Clinical effectiveness was confirmed in bacterial skin and soft tissue infections in dogs and cats and urinary tract infections (cystitis) in dogs associated with bacteria susceptible to marbofloxacin. Bacterial pathogens isolated in clinical field studies are provided in the Microbiology section.

TARGET ANIMAL SAFETY

Dogs

The toxicity of marbofloxacin was assessed in 12- to 14-month-old beagle dogs administered marbofloxacin at 2.5, 7.5 and 12.5 mg/lb/day for 42 days. Vomiting, reddened skin (usually involving the ears) and reddened mucous membranes were occasionally observed in all groups, including controls, but were noted most frequently in the 12.5 mg/lb group. Decreased food consumption and weight loss were significant in the 7.5 mg/lb and 12.5 mg/lb groups. No clinical lameness was noted in any of the treated animals. Minimal to slight lesions in the articular cartilage were observed in 1/8 placebo-treated animals and in 3/8 animals given 12.5 mg marbofloxacin/lb. Macroscopically, these lesions were vesicles, raised areas, or depressed, light-colored areas. Microscopically, these lesions were characterized by the presence of one or more of the following: fissuring, erosion, chondrocyte proliferation, fibrillation, or vertical splitting of the articular cartilage. These cartilage lesions in treated dogs were similar to those in control dogs, and were not typical of those produced by fluoroquinolones. In addition to the above pathologic alterations, red areas of articular cartilage were noted macroscopically in 0/8 placebo-treated dogs and in 2/8 dogs from each of the three marbofloxacin-treated groups. These areas usually correlated microscopically with areas of vascularity of the articular surface, but could not be confirmed microscopically in all animals. They consisted of large blood vessels in mature fibrous connective tissue, with no indication of active vascularization due to drug-induced damage. They were considered most likely to be developmental anomalies or normal variations of the joint surface and were not considered to be related to drug treatment.

Marbofloxacin was administered to 12- to 14-month-old beagle dogs at a dosage of 25 mg/lb/day for 12 days. Decreased food consumption, vomiting, dehydration, excessive salivation, tremors, reddened skin, facial swelling, decreased activity and weight loss were seen in treated dogs. No clinical lameness was noted. As in the 42 day study, grossly visible, focal, red areas of articular cartilage were seen. These findings were noted in 2/6 placebo-treated dogs and in 4/6 marbofloxacintreated dogs. The foci were areas of fibrocartilage with prominent vascularization or increased vascularization of subchondral bone. Due to the appearance microscopically and macroscopically, these red foci were described as likely to be developmental anomalies or normal variations in articular cartilage.

Marbofloxacin administered to 3- to 4-month-old, large breed, purpose-bred mongrel dogs at a dosage of 5 mg/lb/day for 14 days resulted in marked lameness in all dogs due to articular cartilage lesions. Lameness was accompanied by decreased appetite and activity.

Cats

Marbofloxacin was administered for 42 consecutive days to 24 cats approximately 8 months old (8 cats per treatment group) at the dosages of 2.5, 7.5 and 12.5 mg/lb/day (5.5, 16.5 and 27.5 mg/kg/day). Treatment with marbofloxacin did not produce adverse effects on body weights, food consumption, serum chemistry, urinalysis or organ weight parameters. Decreased segmented neutrophil counts were observed in some cats in all treatment groups, including the placebo group, but mean counts were significantly lower in the marbofloxacin-treated groups. In some cats, absolute neutrophil counts were below normal reference values (as low as 615 neutrophils/μL in a marbofloxacin-treated cat and as low as 882 neutrophils/μL in a placebo-treated cat). Other hematological observations were not adversely affected. Clinical signs were occasionally noted in cats in the highest dosage group: excessive salivation in 4/8 cats and redness of ear pinnae in 2/8 cats. Macroscopic changes in the articular cartilage of femurs were seen in one cat receiving 7.5 mg/lb and in 3 cats receiving 12.5 mg/lb. Microscopically, these gross lesions were related to a focal or multifocal chondropathy. Microscopic chondropathy not associated with macroscopic observations was also present in one cat treated with 2.5 mg/lb daily (1X the upper end of the dose range) and one additional cat treated with 7.5 mg/lb daily. There was no evidence of lameness during the course of the study. A perivascular to diffuse dermatitis was seen microscopically in one mid-dose cat and 4 high-dose cats. Funduscopic exam by a board-certified ophthalmologist and histologic examination of retina and optic nerve by ocular pathologists revealed no lesions in any of the treatment groups.

Marbofloxacin was also administered orally to 6 cats approximately 8 months of age for 14 consecutive days at a dosage of 25 mg/lb/day (55 mg/kg/day). Clinical signs associated with drug intolerance were excessive salivation in 5/6 cats and redness of ear pinnae in all cats after 8 days of treatment. Emesis was noted occasionally in several cats and diminished activity was noted in one cat. Decreased food intake was noted in some animals, primarily males, when compared to controls. Perivascular to diffuse dermatitis was seen microscopically in the pinnae of all treated animals and in the standard skin samples of several animals. There was focal or multifocal articular chondropathy in 2/6 treated animals. One treated cat had a duodenal mucosal erosion and one treated cat had a pyloric ulcer. There were no observations of lameness and no adverse effects on hematology, clinical chemistry, urinalysis, or organ weight parameters. Funduscopic examination by a board-certified ophthalmologist and histologic examination of retina and optic nerve by ocular pathologists revealed no lesions.

A study was conducted to investigate the effect of marbofloxacin on articular cartilage of skeletally mature cats 12–14 months of age. Forty cats were randomly assigned to 4 groups of 10 cats each. Groups received placebo or marbofloxacin at dosages of 1.25, 3.75 or 7.5 mg/lb/day (2.75, 8.25 or 16.5 mg/kg/day) for 42 consecutive days. There were no treatment-related pathological changes in the joints or other tissues. Emesis and soft stools was noted in all treatment groups, including placebo, and increased in frequency with increasing dose and duration of treatment. Emesis was more apparent in the high-dose males.

STORAGE CONDITIONS

Store below 30°C (86°F).

HOW SUPPLIED

Zeniquin tablets are available in the following strengths of marbofloxacin and bottle sizes:

25 mg scored tablets supplied in bottles that contain 100 or 250 tablets
50 mg scored tablets supplied in bottles that contain 100 or 250 tablets
100 mg scored tablets supplied in a 50 tablet bottle
200 mg scored tablets supplied in a 50 tablet bottle

REFERENCES

1. Schneider M, et al: Pharmacokinetics of marbofloxacin in dogs after oral and parenteral administration. J Vet Pharmacol Therap 19:56–61, 1996.

To report suspected adverse effects, and/or obtain a copy of the MSDS, call 1-888-963-8471.

Approved by FDA under NADA # 141-151

zoetis

Distributed by:
Zoetis Inc.
Kalamazoo, MI 49007

40027358
Revised: May 2019

PRINCIPAL DISPLAY PANEL - 25 mg Bottle Label

Zeniquin®
(marbofloxacin)

Tablets

For oral use in dogs and cats only

Antibacterial

Caution: Federal law restricts
this drug to use by or on the
order of a licensed veterinarian.

Federal law prohibits the
extralabel use of this drug
in food-producing animals.

25 mg

100 Tablets

Approved by FDA under NADA # 141-151

zoetis